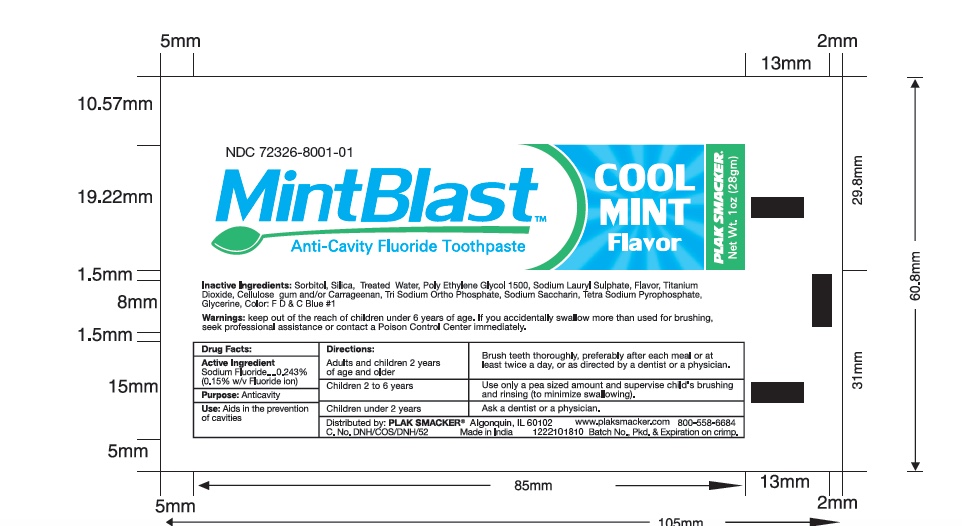 DRUG LABEL: MINTBLAST
NDC: 72326-8001 | Form: PASTE
Manufacturer: YOUNG PS ACQUISITION, LLC
Category: otc | Type: HUMAN OTC DRUG LABEL
Date: 20211123

ACTIVE INGREDIENTS: SODIUM FLUORIDE 2.43 mg/1 g
INACTIVE INGREDIENTS: SORBITOL; SILICON DIOXIDE; WATER; GLYCERIN; SODIUM LAURYL SULFATE; TITANIUM DIOXIDE; SACCHARIN SODIUM; CARBOXYMETHYLCELLULOSE SODIUM, UNSPECIFIED FORM; POLYETHYLENE GLYCOL 1500; CARRAGEENAN; SODIUM PHOSPHATE, TRIBASIC, ANHYDROUS; SODIUM PYROPHOSPHATE; FD&C BLUE NO. 1

MINTBLAST ANTICAVITY FLUORIDE TOOTH PASTE

Active ingredient

Sodium Fluoride -0.243 mg (0.15% w/v Fluoride ion)

Purpose

Anticavity

Use

Aids in the prevention of cavities.

Directions :

- Adults and children 2 years of age and older: Brush teeth thoroughly, preferably after each meal or at least twice a day, or use as directed by a dentist or a physician.
- Children 2 to 6 years: Use only a pea sized amount and supervise child's brushing and rinsing (to minimize swallowing) .
- Children under 2 year : Ask a dentist or physician .

Warnings

Keep out of the reach of children under 6 years of age. If you accidentally swallow more than used for brushing, seek professional assistance or contact a Poison Control Center immediately.

Inactive Ingredients

Sorbitol, Silica , Treated Water , Poly Ethylene Glycol 1500 , Sodium Lauryl Sulfate , Flavor, Titanium Dioxide , Cellulose Gum and/or Carrageenan, Tri Sodium Ortho Phosphate, Saccharin Sodium, Tetra Sodium Pyrophosphate,Glycerine, Color : FD&C Blue No.1